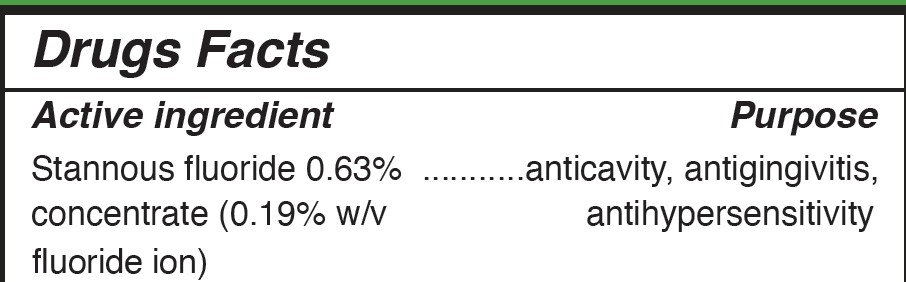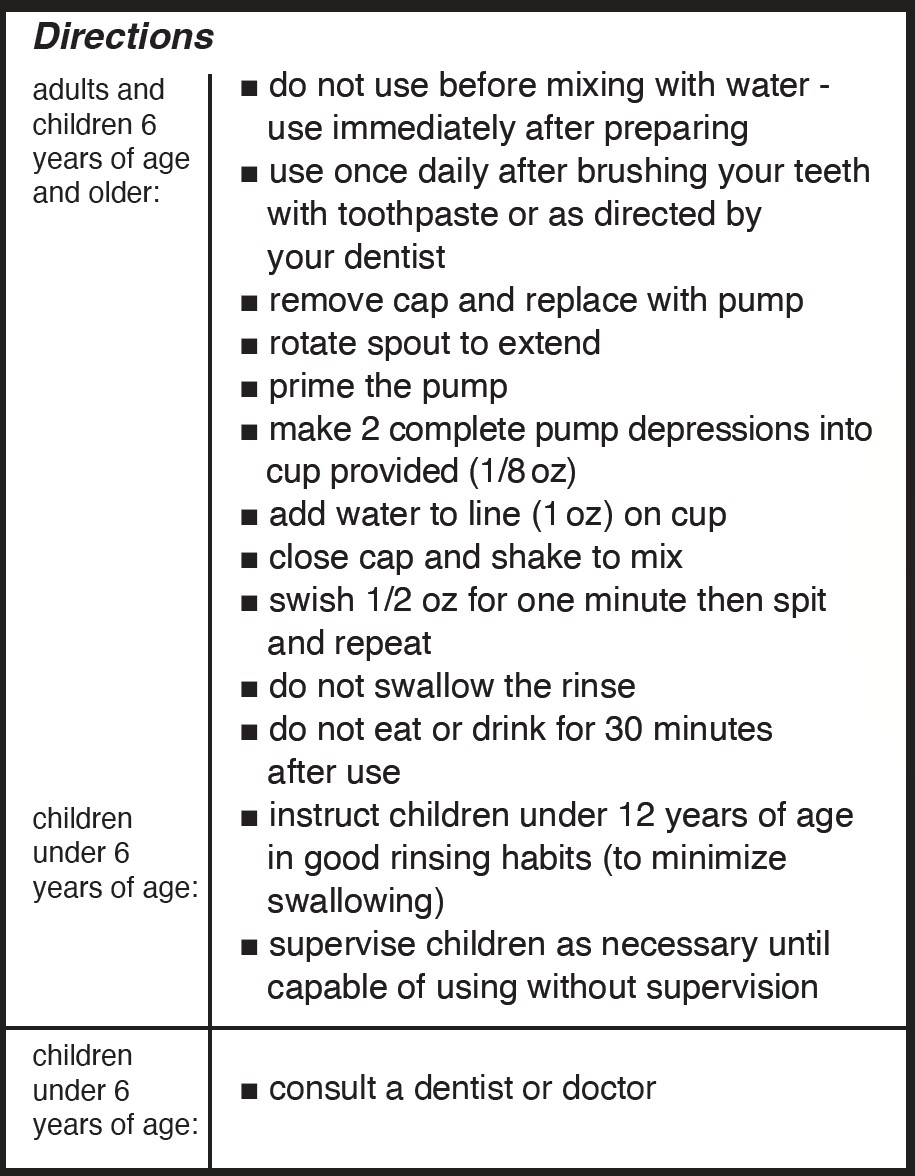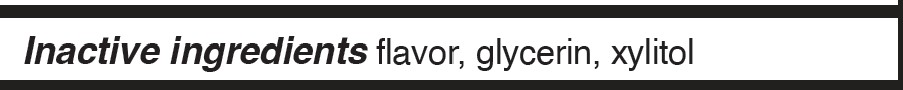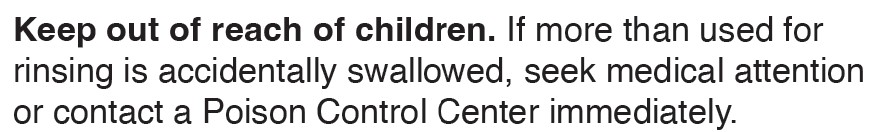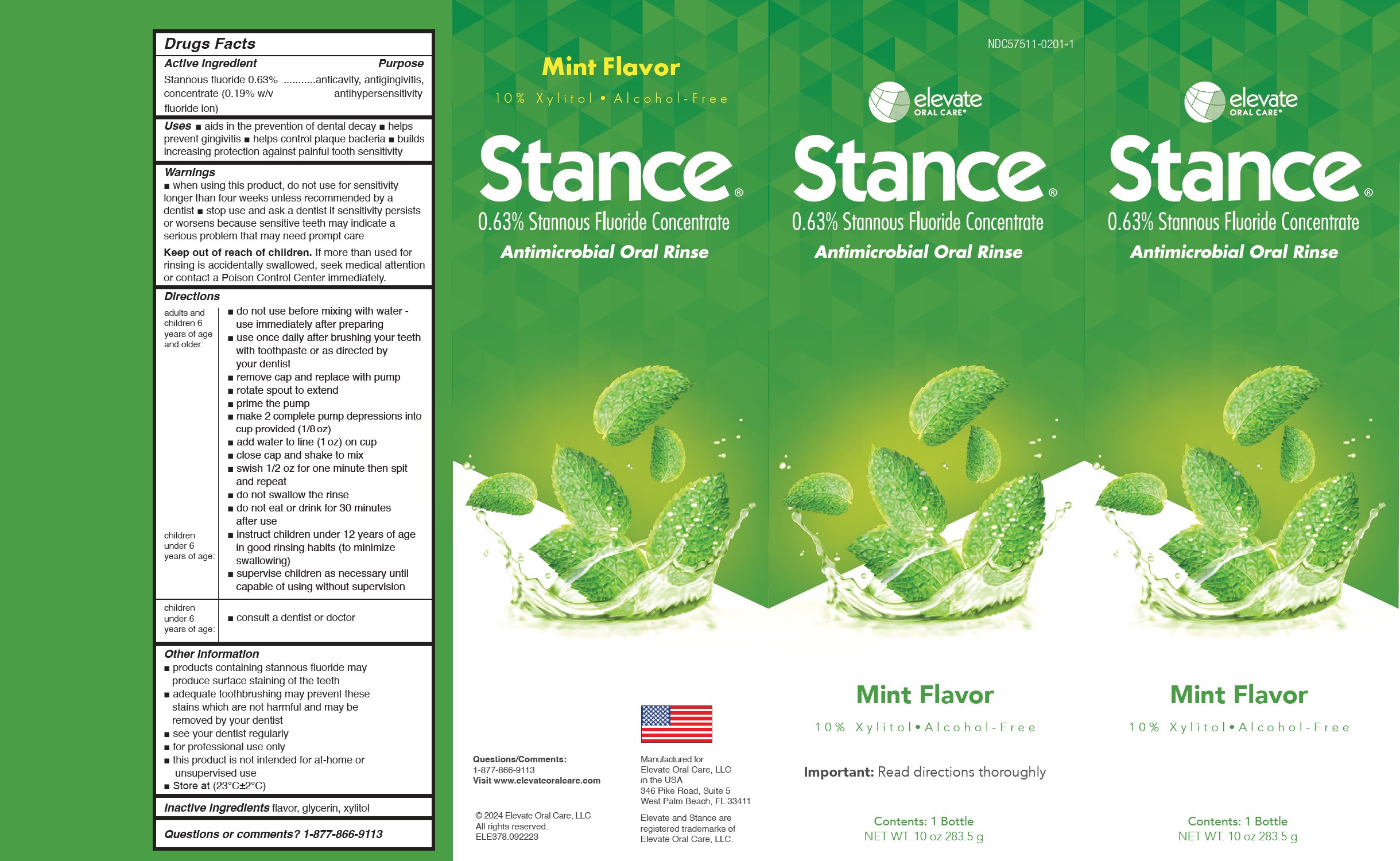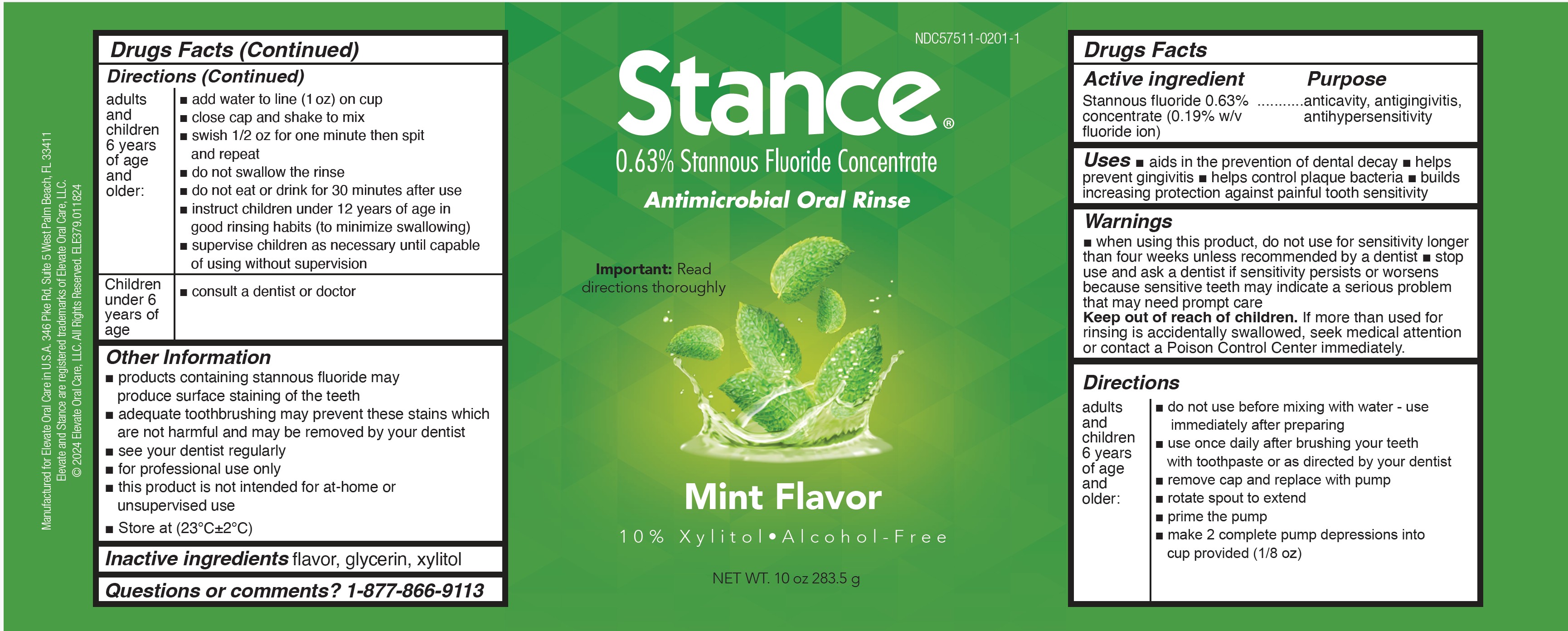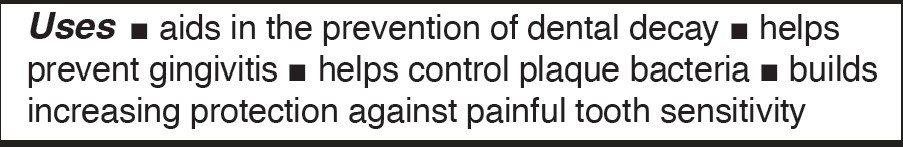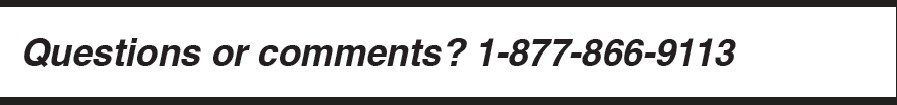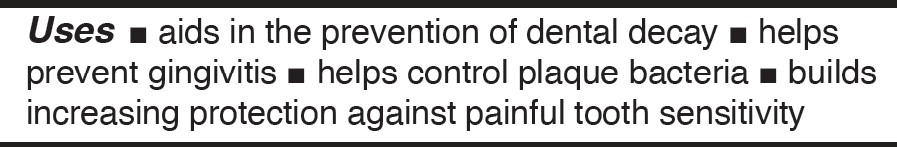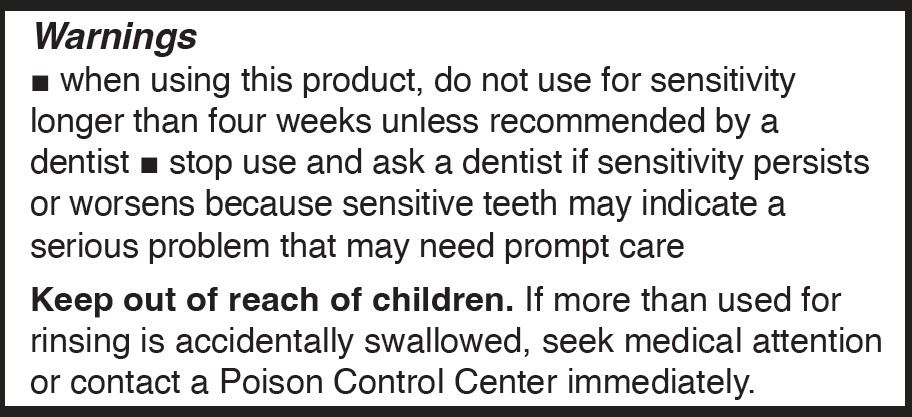 DRUG LABEL: Stance
NDC: 57511-0201 | Form: RINSE
Manufacturer: Elevate Oral Care
Category: otc | Type: HUMAN OTC DRUG LABEL
Date: 20250922

ACTIVE INGREDIENTS: STANNOUS FLUORIDE 1.2 mg/1 mL
INACTIVE INGREDIENTS: GLYCERIN; XYLITOL

Stance 0.63% Stannous Fluoride Concentrate Rinse Mint

Dosage and Administration

make 2 complete pump depressions into cup
provided (1/8 oz)
• add tap water to line (1 oz) on cup
• close cap and shake to mix
• vigorously swish 1/2 oz for one minute then
spit out and repeat with second 1/2 oz
• do not swallow the rinse